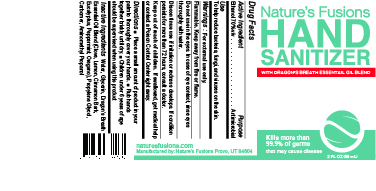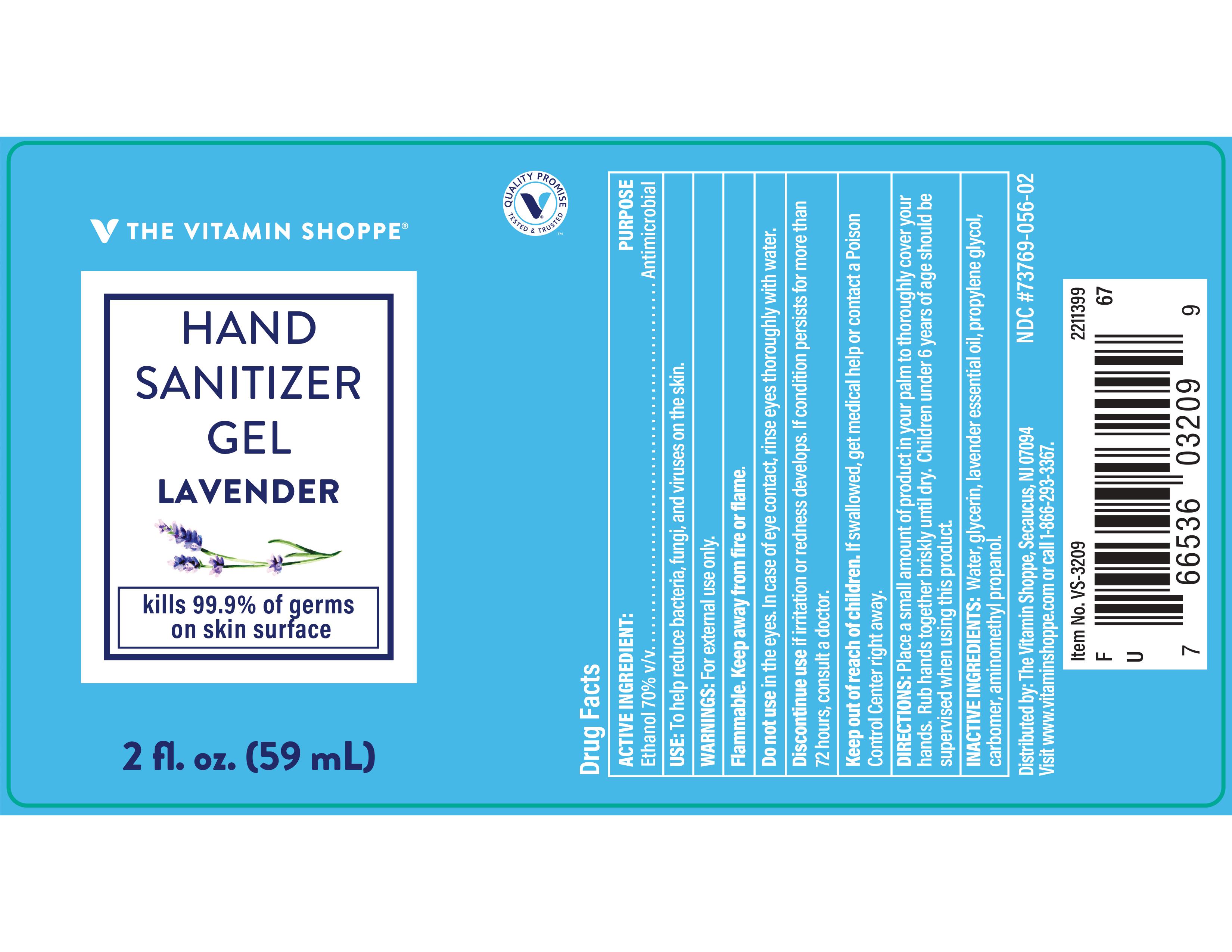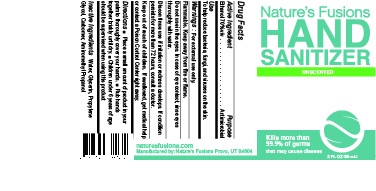 DRUG LABEL: Unscented Hand Sanitizer Gel
NDC: 73769-050 | Form: GEL
Manufacturer: NATURE'S FUSIONS, LLC
Category: otc | Type: HUMAN OTC DRUG LABEL
Date: 20240531

ACTIVE INGREDIENTS: ALCOHOL 69.8 mL/100 mL
INACTIVE INGREDIENTS: WATER; PROPYLENE GLYCOL; AMINOMETHYLPROPANOL; CARBOMER HOMOPOLYMER, UNSPECIFIED TYPE; GLYCERIN

Hand Sanitizer Gel

PACKAGE LABEL

Gel with dragon's breath

Lavender gel